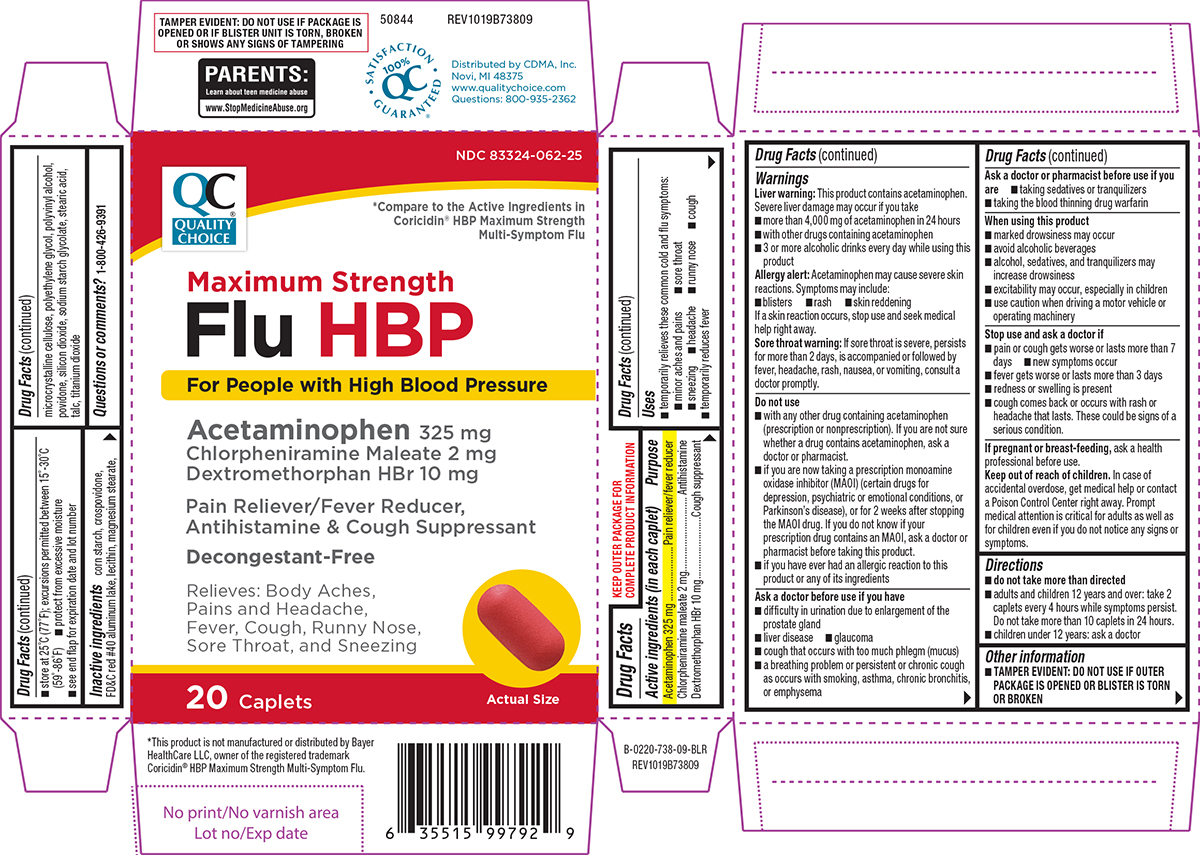 DRUG LABEL: Flu HBP
NDC: 83324-062 | Form: TABLET, FILM COATED
Manufacturer: Chain Drug Marketing Association, Inc.
Category: otc | Type: HUMAN OTC DRUG LABEL
Date: 20260217

ACTIVE INGREDIENTS: ACETAMINOPHEN 325 mg/1 1; CHLORPHENIRAMINE MALEATE 2 mg/1 1; DEXTROMETHORPHAN HYDROBROMIDE 10 mg/1 1
INACTIVE INGREDIENTS: STARCH, CORN; CROSPOVIDONE, UNSPECIFIED; FD&C RED NO. 40 ALUMINUM LAKE; LECITHIN, SOYBEAN; MAGNESIUM STEARATE; MICROCRYSTALLINE CELLULOSE; POLYETHYLENE GLYCOL, UNSPECIFIED; POLYVINYL ALCOHOL, UNSPECIFIED; POVIDONE, UNSPECIFIED; SILICON DIOXIDE; SODIUM STARCH GLYCOLATE TYPE A POTATO; STEARIC ACID; TALC; TITANIUM DIOXIDE

Quality Choice 44-738

Active ingredients (in each caplet)

Acetaminophen 325 mg
Chlorpheniramine maleate 2 mg
Dextromethorphan HBr 10 mg

Purpose

Pain reliever/fever reducer
Antihistamine
Cough suppressant

Uses

- temporarily relieves these common cold and flu symptoms:
  - minor aches and pains
  - sore throat
  - sneezing
  - headache
  - runny nose
  - cough
- temporarily reduces fever

Warnings

Liver warning: This product contains acetaminophen. Severe liver damage may occur if you take

- more than 4,000 mg of acetaminophen in 24 hours
- with other drugs containing acetaminophen
- 3 or more alcoholic drinks every day while using this product

Allergy alert: Acetaminophen may cause severe skin reactions. Symptoms may include:

- blisters
- rash
- skin reddening

If a skin reaction occurs, stop use and seek medical help right away.

Sore throat warning: If sore throat is severe, persists for more than 2 days, is accompanied or followed by fever, headache, rash, nausea, or vomiting, consult a doctor promptly.

Do not use

- with any other drug containing acetaminophen (prescription or nonprescription). If you are not sure whether a drug contains acetaminophen, ask a doctor or pharmacist.
- if you are now taking a prescription monoamine oxidase inhibitor (MAOI) (certain drugs for depression, psychiatric or emotional conditions, or Parkinson's disease), or for 2 weeks after stopping the MAOI drug. If you do not know if your prescription drug contains an MAOI, ask a doctor or pharmacist before taking this product.
- if you have ever had an allergic reaction to this product or any of its ingredients

Ask a doctor before use if you have

- difficulty in urination due to enlargement of the prostate gland
- liver disease
- cough that occurs with too much phlegm (mucus)
- glaucoma
- a breathing problem or persistent or chronic cough as occurs with smoking, asthma, chronic bronchitis, or emphysema

Ask a doctor or pharmacist before use if you are

- taking the blood thinning drug warfarin
- taking sedatives or tranquilizers

When using this product

- avoid alcoholic beverages
- marked drowsiness may occur
- alcohol, sedatives, and tranquilizers may increase drowsiness
- excitability may occur, especially in children
- use caution when driving a motor vehicle or operating machinery

Stop use and ask a doctor if

- pain or cough gets worse or lasts more than 7 days
- new symptoms occur
- fever gets worse or lasts more than 3 days
- redness or swelling is present
- cough comes back or occurs with rash or headache that lasts. These could be signs of a serious condition.

If pregnant or breast-feeding,

ask a health professional before use.

Keep out of reach of children.

In case of accidental overdose, get medical help or contact a Poison Control Center right away. Prompt medical attention is critical for adults as well as for children even if you do not notice any signs or symptoms.

Directions

- do not take more than directed
- adults and children 12 years and over: take 2 caplets every 4 hours while symptoms persist. Do not take more than 10 caplets in 24 hours.
- children under 12 years: ask a doctor

Other information

- TAMPER EVIDENT: DO NOT USE IF OUTER PACKAGE IS OPENED OR BLISTER IS TORN OR BROKEN
- store at 25°C (77°F); excursions permitted between 15°-30°C (59°-86°F)
- see end flap for expiration date and lot number
- protect from excessive moisture

Inactive ingredients

corn starch, crospovidone, FD&C red #40 aluminum lake, lecithin, magnesium stearate, microcrystalline cellulose, polyethylene glycol, polyvinyl alcohol, povidone, silicon dioxide, sodium starch glycolate, stearic acid, talc, titanium dioxide

Questions or comments?

1-800-426-9391

Principal Display Panel

QC®
QUALITY
CHOICE

NDC 83324-062-25

*Compare to the Active Ingredients in
Coricidin® HBP Maximum Strength
Multi-Symptom Flu

Maximum Strength
Flu HBP

For People with High Blood Pressure

Acetaminophen 325 mg
Chlorpheniramine Maleate 2 mg
Dextromethorphan HBr 10 mg
Pain Reliever/Fever Reducer,
Antihistamine & Cough Suppressant

Decongestant-Free

Relieves: Body Aches,
Pains and Headache,
Fever, Cough, Runny Nose,
Sore Throat, and Sneezing

Actual Size

20 Caplets

TAMPER EVIDENT: DO NOT USE IF PACKAGE IS
OPENED OR IF BLISTER UNIT IS TORN, BROKEN
OR SHOWS ANY SIGNS OF TAMPERING

*This product is not manufactured or distributed by Bayer
HealthCare LLC, owner of the registered trademark
Coricidin® HBP Maximum Strength Multi-Symptom Flu.

50844 REV1019B73809

Distributed by CDMA, Inc.
Novi, MI 48375
www.qualitychoice.com
Questions: 800-935-2362

SATISFACTION
100%
QC
GUARANTEED

Quality Choice 44-738